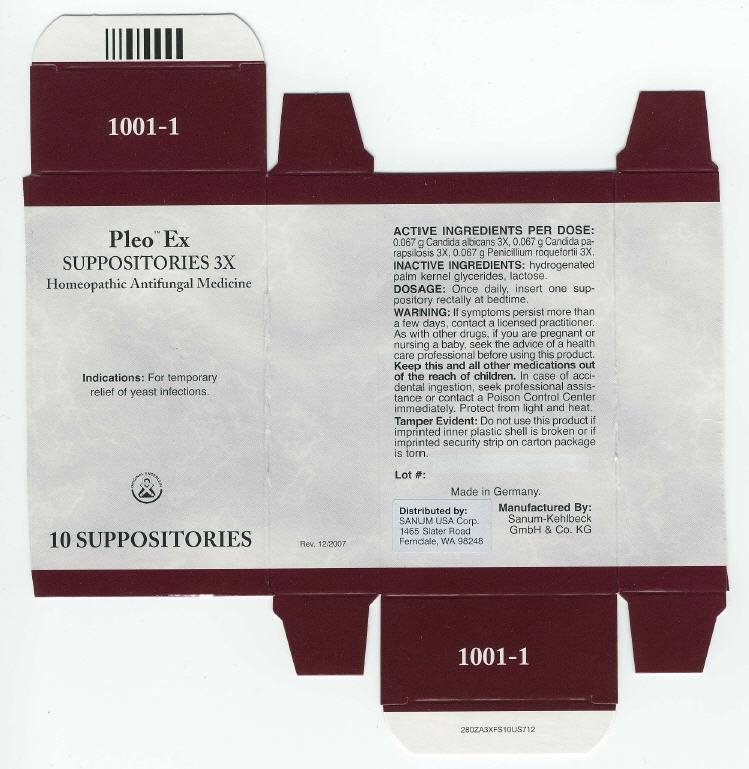 DRUG LABEL: Pleo Ex
NDC: 60681-1001 | Form: SUPPOSITORY
Manufacturer: Sanum Kehlbeck GmbH & Co. KG
Category: homeopathic | Type: HUMAN OTC DRUG LABEL
Date: 20091013

ACTIVE INGREDIENTS: candida albicans 3 [HP_X]/1 1; candida parapsilosis 3 [HP_X]/1 1; penicillium roqueforti 3 [HP_X]/1 1
INACTIVE INGREDIENTS: lactose

Pleo™ Ex
SUPPOSITORIES 3X

Homeopathic Antifungal Medicine

10 SUPPOSITORIES

Indications

For temporary relief of yeast infections.

ACTIVE INGREDIENTS PER DOSE

0.067 g Candida albicans 3X, 0.067 g Candida parapsilosis 3X, 0.067 g Penicillium roquefortii 3X.

INACTIVE INGREDIENTS

hydrogenated palm kernel glycerides, lactose.

DOSAGE

Once daily, insert one suppository rectally at bedtime.

WARNING

If symptoms persist more than a few days, contact a licensed practitioner. As with other drugs, if you are pregnant or nursing a baby, seek the advice of a health care professional before using this product.

KEEP OUT OF REACH OF CHILDREN

Keep this and all other medications out of the reach of children. In case of accidental ingestion, seek professional assistance or contact a Poison Control Center immediately.

STORAGE AND HANDLING

Protect from light and heat.

Tamper Evident

Do not use this product if imprinted inner plastic shell is broken or if imprinted security strip on carton package is torn.

Made in Germany.

Distributed by:
SANUM USA Corp.
1465 Slater Road
Ferndale, WA 98248

Manufactured By:
Sanum-Kehlbeck
GmbH & Co. KG

Rev. 12/2007

PRINCIPAL DISPLAY PANEL - 10 Suppositories Carton

Pleo™ Ex
SUPPOSITORIES 3X

Homeopathic Antifungal Medicine

Indications: For temporary
relief of yeast infections.

ORIGINAL ENDERLEIN

10 SUPPOSITORIES